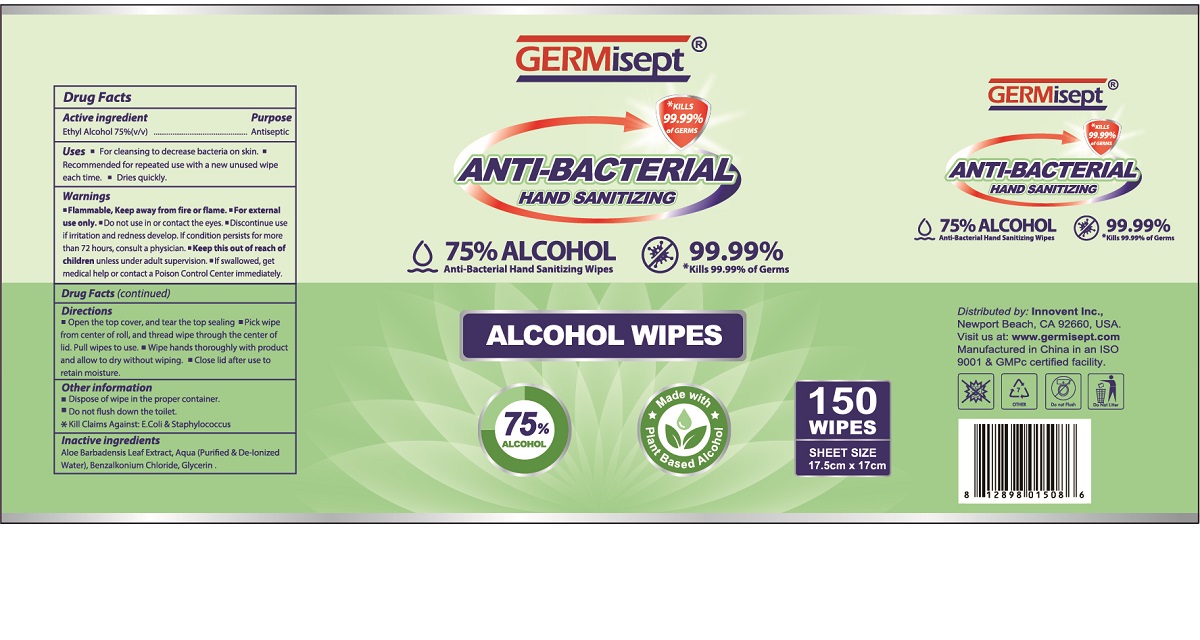 DRUG LABEL: Germisept Antibacterial Alcohol Wipes
NDC: 75127-103 | Form: CLOTH
Manufacturer: Jurong Dongfa General Merchandise Co., Ltd.
Category: otc | Type: HUMAN OTC DRUG LABEL
Date: 20220224

ACTIVE INGREDIENTS: ALCOHOL 0.75 mL/1 g
INACTIVE INGREDIENTS: ALOE VERA LEAF; WATER; BENZALKONIUM CHLORIDE; GLYCERIN

75127-103 Germisept Antibacterial Alcohol Wipes 150 wipes 75% Ethyl Alcohol

Active ingredient

Ethyl Alcohol 75%(v/v)

Purpose

Antiseptic

Uses:

- For cleansing to decrease bacteria on skin.
- Recommended for repeated use with a new unused wipe each time.
- Dries quickly.

Warnings

- Flammable,Keep away from fire or flame.
- For external use only.

Do not use

- in or contact the eyes.
- Discontinue use if irritation and redness develop. If condition persists for more than 72 hours, consult a physician.

Keep this out of reach of children.

- unless under adult supervision.
- If swallowed, get medical help or contact a Poison Control Center immediately.

Directions

- Open the flip top lid, remove one wipe to use.
- Wipe hands thoroughly with product and allow to dry without wiping.
- Close filp top lid label after use to retain moisture.

Other information

- Dispose of wipe in the proper container.
- Do not flush down the toilet.

Inactive ingredients

Aloe Barbadensis Leaf Extract, Aqua (Purified & De-Ionized Water), Benzalkonium Chloride, Glycerin.